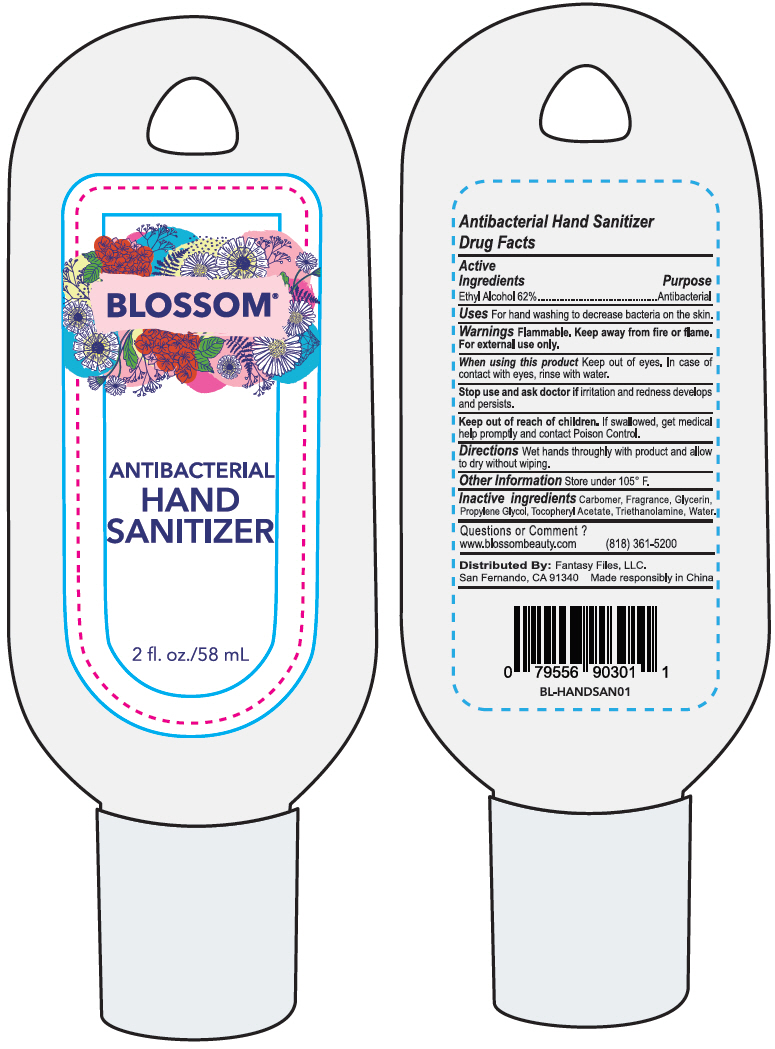 DRUG LABEL: BLOSSOM ANTIBACTERIAL HAND SANITIZER
NDC: 80583-110 | Form: GEL
Manufacturer: FANTASY FILES, LLC
Category: otc | Type: HUMAN OTC DRUG LABEL
Date: 20210209

ACTIVE INGREDIENTS: Alcohol 62 mL/100 mL
INACTIVE INGREDIENTS: CARBOMER HOMOPOLYMER, UNSPECIFIED TYPE; GLYCERIN; PROPYLENE GLYCOL; .ALPHA.-TOCOPHEROL ACETATE; TROLAMINE; WATER

BLOSSOM® ANTIBACTERIAL HAND SANITIZER

Drug Facts

Active Ingredients

Ethyl Alcohol 62%

Purpose

Antibacterial

Uses

For hand washing to decrease bacteria on skin.

Warnings

Flammable. Keep away from fire or flame.

For external use only.

When using this product

Keep out of eyes. In case of contact with eyes rinse with water.

Stop use and ask doctor if irritation and redness develops and persists.

Keep out of reach of children. If swallowed, get medical help promptly and contact Poison Control.

Directions

Wet hands thoroughly with product and allow to dry without wiping.

Other Information

Store under 105° F

Inactive Ingredients

Carbomer, Fragrance, Glycerin, Propylene Glycol, Tocopheryl Acetate, Triethanolamine, Water.

Questions or Comment?

www.blossombeauty.com
(818) 361-5200

Distributed By: Fantasy Files, LLC
San Fernando, CA 91340

PRINCIPAL DISPLAY PANEL - 58 mL Bottle Label

BLOSSOM®

ANTIBACTERIAL
HAND
SANITIZER

2 fl. oz./58 mL